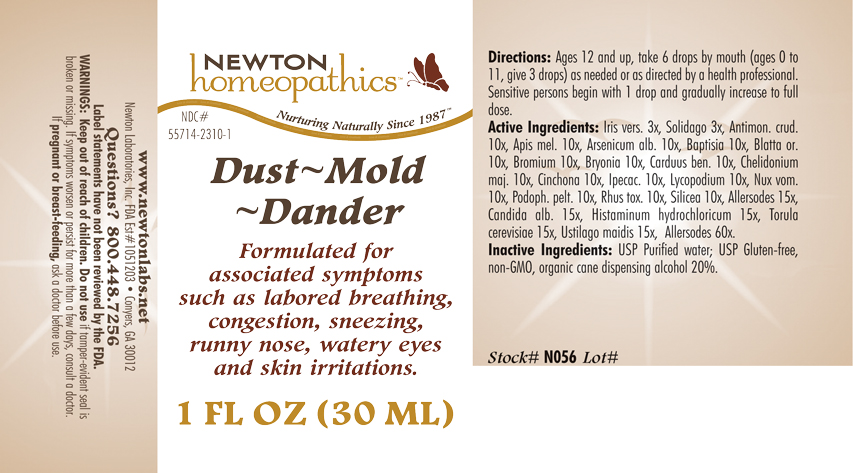 DRUG LABEL: Dust - Mold - Dander 
NDC: 55714-2310 | Form: LIQUID
Manufacturer: Newton Laboratories, Inc.
Category: homeopathic | Type: HUMAN OTC DRUG LABEL
Date: 20110301

ACTIVE INGREDIENTS: Felis Catus Skin 60 [hp_X]/1 mL; Canis Lupus Familiaris Skin 60 [hp_X]/1 mL; Oryctolagus Cuniculus Skin 60 [hp_X]/1 mL; Equus Caballus Skin 60 [hp_X]/1 mL; Serinus Canaria Feather 60 [hp_X]/1 mL; Gallus Gallus Feather 60 [hp_X]/1 mL; Anas Platyrhynchos Feather 60 [hp_X]/1 mL; Anser Anser Feather 60 [hp_X]/1 mL; Melopsittacus Undulatus Feather 60 [hp_X]/1 mL; Phasianus Colchicus Feather 60 [hp_X]/1 mL; Meleagris Gallopavo Feather 60 [hp_X]/1 mL; Felis Catus Hair 60 [hp_X]/1 mL; Human Dander 60 [hp_X]/1 mL; Canis Lupus Familiaris Hair 60 [hp_X]/1 mL; Equus Caballus Hair 60 [hp_X]/1 mL; Oryctolagus Cuniculus Hair 60 [hp_X]/1 mL; Human Hair 60 [hp_X]/1 mL; Human Skin 60 [hp_X]/1 mL; Sheep Wool 60 [hp_X]/1 mL; Bos Taurus Hair 60 [hp_X]/1 mL; Capra Hircus Hair 60 [hp_X]/1 mL; Cavia Porcellus Hair 60 [hp_X]/1 mL; Mesocricetus Auratus Hair 60 [hp_X]/1 mL; Wheat Gluten 15 [hp_X]/1 mL; Aspergillus Niger Var. Niger 15 [hp_X]/1 mL; Cladosporium Herbarum 15 [hp_X]/1 mL; House Dust 15 [hp_X]/1 mL; Candida Albicans 15 [hp_X]/1 mL; Histamine Dihydrochloride 15 [hp_X]/1 mL; Saccharomyces Cerevisiae 15 [hp_X]/1 mL; Ustilago Maydis 15 [hp_X]/1 mL; Antimony Trisulfide 10 [hp_X]/1 mL; Apis Mellifera 10 [hp_X]/1 mL; Arsenic Trioxide 10 [hp_X]/1 mL; Baptisia Tinctoria Root 10 [hp_X]/1 mL; Blatta Orientalis 10 [hp_X]/1 mL; Bromine 10 [hp_X]/1 mL; Bryonia Alba Root 10 [hp_X]/1 mL; Centaurea Benedicta 10 [hp_X]/1 mL; Chelidonium Majus 10 [hp_X]/1 mL; Cinchona Officinalis Bark 10 [hp_X]/1 mL; Ipecac 10 [hp_X]/1 mL; Lycopodium Clavatum Spore 10 [hp_X]/1 mL; Strychnos Nux-vomica Seed 10 [hp_X]/1 mL; Podophyllum 10 [hp_X]/1 mL; Toxicodendron Pubescens Leaf 10 [hp_X]/1 mL; Silicon Dioxide 10 [hp_X]/1 mL; Iris Versicolor Root 3 [hp_X]/1 mL; Solidago Virgaurea Flowering Top 3 [hp_X]/1 mL
INACTIVE INGREDIENTS: Alcohol; Water

Dust - Mold - Dander

INDICATIONS & USAGE SECTION

Formulated for associated symptoms such as labored breathing, congestion, sneezing, runny nose, watery eyes and skin irritations.

DOSAGE & ADMINISTRATION SECTION

Directions: Ages 12 and up, take 6 drops by mouth (ages 0 to 11, give 3 drops) as needed or as directed by a health professional. Sensitive persons begin with 1 drop and gradually increase to full dose.

OTC - ACTIVE INGREDIENT SECTION

Allersodes 60x, Allersodes 15x, Candida alb. 15x, Histaminum hydrochloricum 15x, Torula cerevisiae 15x, Ustilago maidis 15x, Antimon. crud. 10x, Apis mel. 10x, Arsenicum alb. 10x, Baptisia 10x, Blatta orientalis 10x, Bromium 10x, Bryonia 10x, Carduus ben. 10x, Chelidonium maj. 10x, Cinchona 10x, Ipecac. 10x, Lycopodium 10x, Nux vom. 10x, Podoph. pelt. 10x, Rhus tox. 10x, Silicea 10x, Iris versicolor 3x, Solidago 3x.

OTC - PURPOSE SECTION

Formulated for associated symptoms such as labored breathing, congestion, sneezing, runny nose, watery eyes and skin irritations.

INACTIVE INGREDIENT SECTION

Inactive Ingredients: USP Purified Water; USP Gluten-free, non-GMO, organic cane dispensing alcohol 20%.

QUESTIONS SECTION

www.newtonlabs.net Newton Laboratories, Inc. FDA Est # 1051203 - Conyers, GA 30012
Questions? 1.800.448.7256

WARNINGS SECTION

Warning: Keep our of reach of children. Do not use if tamper-evident seal is broken or missing. If symptoms worsen or persist for more than a few days, consult a doctor. If pregnant or breast-feeding, ask a doctor before use.

OTC - PREGNANCY OR BREAST FEEDING SECTION

If pregnant or breast-feeding, ask a doctor before use.

OTC - KEEP OUT OF REACH OF CHILDREN SECTION

Keep out of reach of children.